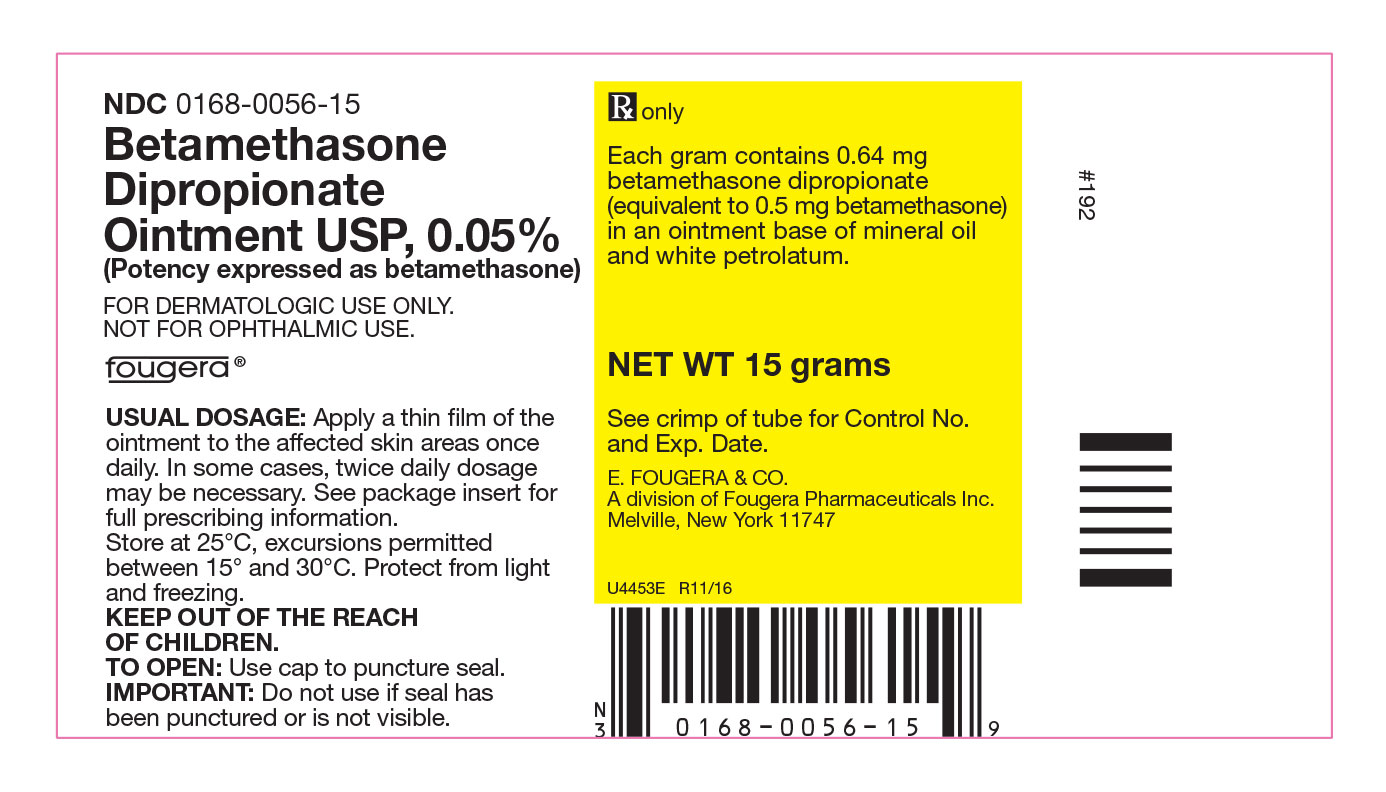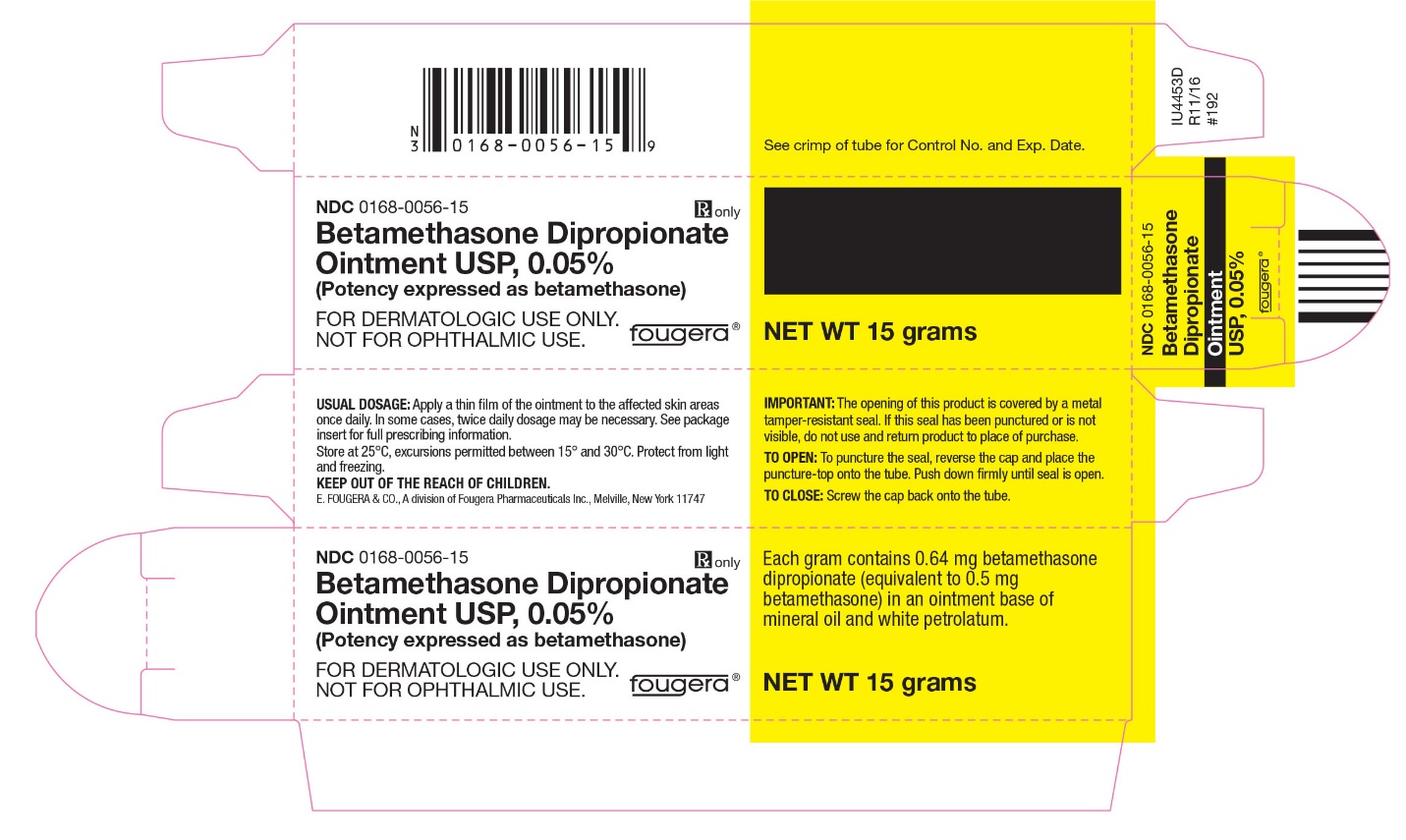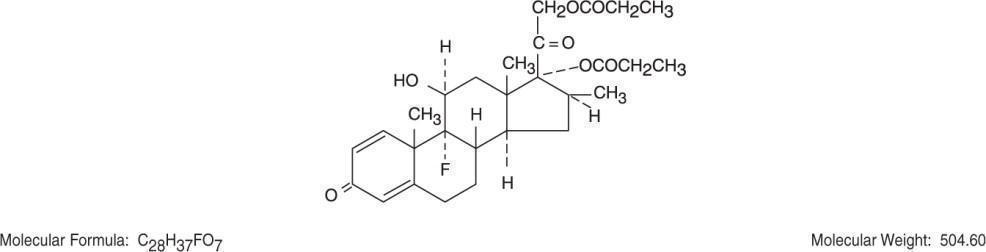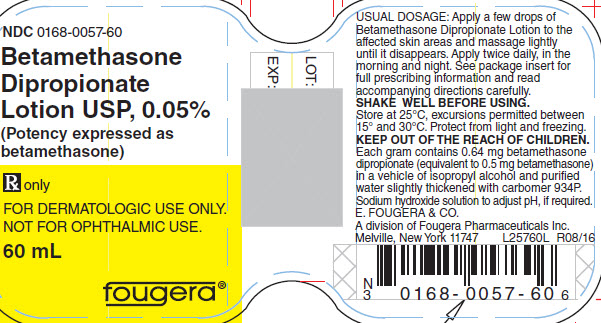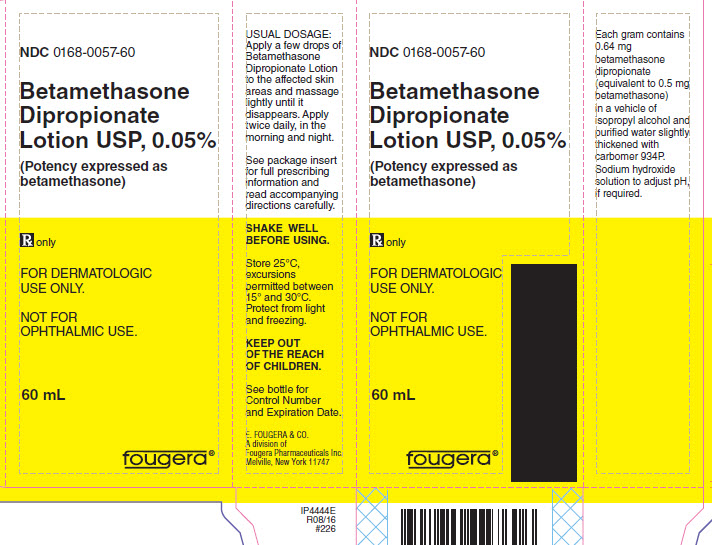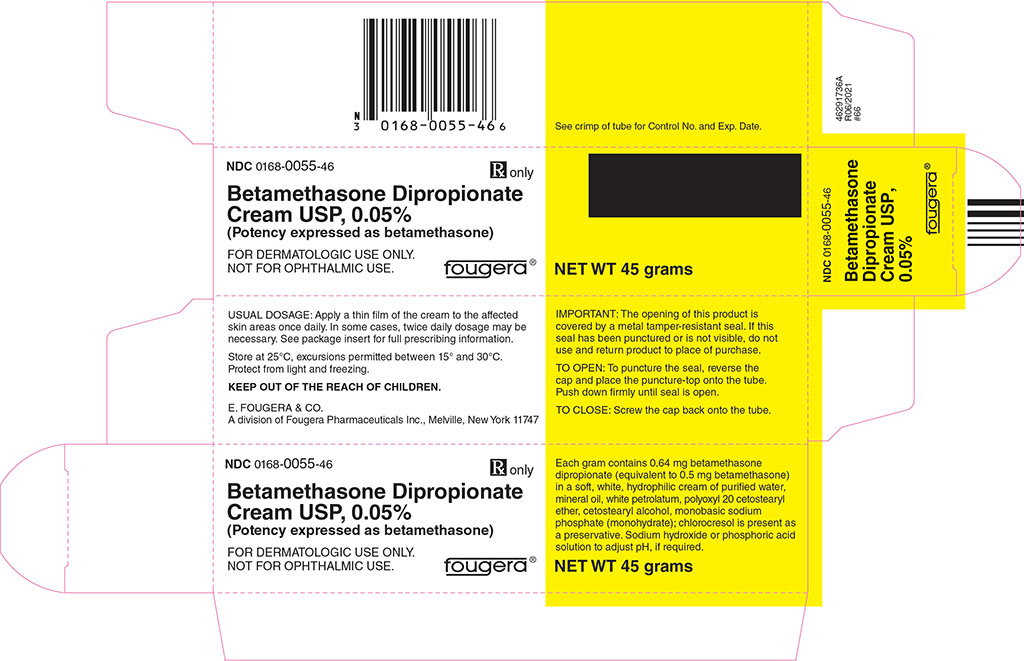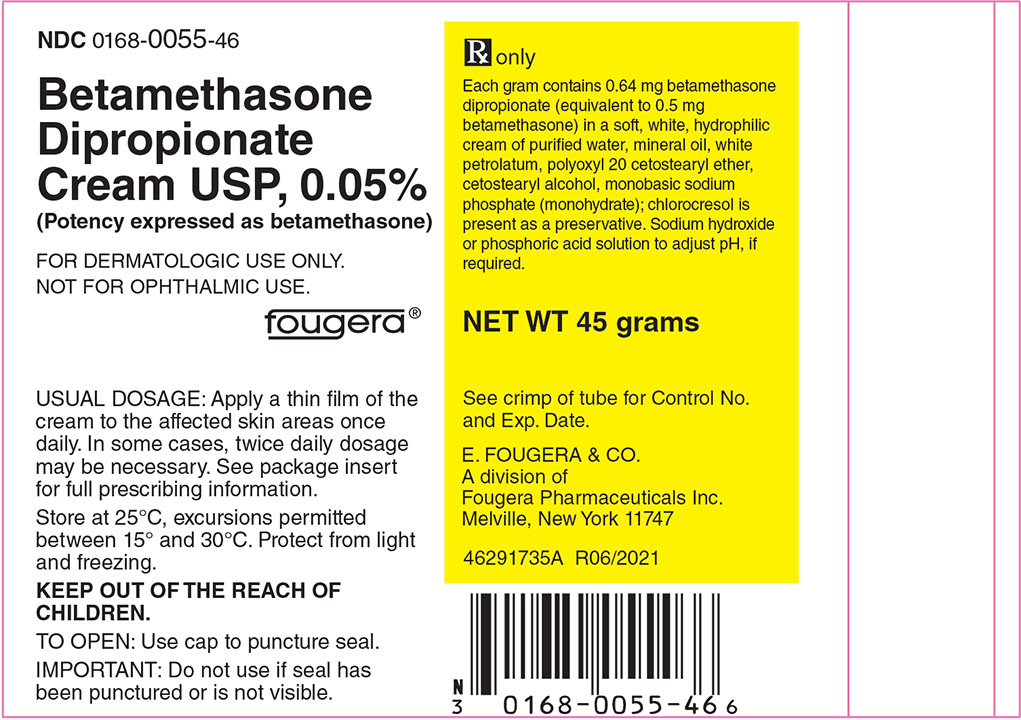 DRUG LABEL: Betamethasone Dipropionate
NDC: 0168-0055 | Form: CREAM
Manufacturer: E. Fougera & Co. a division of Fougera Pharmaceuticals Inc.
Category: prescription | Type: HUMAN PRESCRIPTION DRUG LABEL
Date: 20260128

ACTIVE INGREDIENTS: betamethasone dipropionate 0.5 mg/1 g
INACTIVE INGREDIENTS: WATER; MINERAL OIL; PETROLATUM; POLYOXYL 20 CETOSTEARYL ETHER; CETOSTEARYL ALCOHOL; SODIUM PHOSPHATE, MONOBASIC, UNSPECIFIED FORM; PHOSPHORIC ACID; SODIUM HYDROXIDE; CHLOROCRESOL

BETAMETHASONE DIPROPIONATE CREAM USP, 0.05%
BETAMETHASONE DIPROPIONATE OINTMENT USP, 0.05%
BETAMETHASONE DIPROPIONATE LOTION USP, 0.05%

(Potency expressed as betamethasone)

Rx only

FOR DERMATOLOGIC USE ONLY.
NOT FOR OPHTHALMIC USE.

DESCRIPTION:

Betamethasone Dipropionate Cream, Ointment and Lotion contain betamethasone dipropionate USP, a synthetic adrenocorticosteroid, for dermatologic use. Betamethasone, an analog of prednisolone, has a high degree of glucocorticoid activity and a slight degree of mineralocorticoid activity.

Betamethasone dipropionate is a white to cream white odorless crystalline powder insoluble in water. Chemically, it is 9-fluoro-11β,17,21-trihydroxy-16β-methylpregna-1,4-diene-3,20-dione 17,21-dipropionate. The structural formula is:

Each gram of the 0.05% Cream contains 0.64 mg betamethasone dipropionate (equivalent to 0.5 mg betamethasone) in a soft, white, hydrophilic cream of purified water, mineral oil, white petrolatum, polyoxyl 20 cetostearyl ether, cetostearyl alcohol, monobasic sodium phosphate (monohydrate); chlorocresol is present as a preservative. Sodium hydroxide or phosphoric acid solution to adjust pH, if required.

Each gram of the 0.05% Ointment contains 0.64 mg betamethasone dipropionate (equivalent to 0.5 mg betamethasone) in an ointment base of mineral oil and white petrolatum.

Each gram of the 0.05% Lotion contains 0.64 mg betamethasone dipropionate (equivalent to 0.5 mg betamethasone) in a vehicle of isopropyl alcohol and purified water slightly thickened with carbomer 934P. Sodium hydroxide solution to adjust pH, if required.

CLINICAL PHARMACOLOGY:

Topical corticosteroids share anti-inflammatory, anti-pruritic and vasoconstrictive actions.

The mechanism of anti-inflammatory activity of the topical corticosteroids is unclear. Various laboratory methods, including vasoconstrictor assays, are used to compare and predict potencies and/or clinical efficacies of the topical corticosteroids. There is some evidence to suggest that a recognizable correlation exists between vasoconstrictor potency and therapeutic efficacy in man.

Pharmacokinetics: The extent of percutaneous absorption of topical corticosteroids is determined by many factors including the vehicle, the integrity of the epidermal barrier, and the use of occlusive dressings.

Topical corticosteroids can be absorbed from normal intact skin. Inflammation and/or other disease processes in the skin increase percutaneous absorption. Occlusive dressings substantially increase the percutaneous absorption of topical corticosteroids (See DOSAGE AND ADMINISTRATION).

Once absorbed through the skin, topical corticosteroids are handled through pharmacokinetic pathways similar to systemically administered corticosteroids. Corticosteroids are bound to plasma proteins in varying degrees. Corticosteroids are metabolized primarily in the liver and are then excreted by the kidneys. Some of the topical corticosteroids and their metabolites are also excreted into the bile.

INDICATIONS AND USAGE:

Topical corticosteroids are indicated for the relief of the inflammatory and pruritic manifestations of corticosteroid-responsive dermatoses.

CONTRAINDICATIONS:

Topical corticosteroids are contraindicated in those patients with a history of hypersensitivity to any of the components of the preparation.

PRECAUTIONS:

GENERAL PRECAUTIONS

General: Systemic absorption of topical corticosteroids has produced reversible hypothalamic-pituitary-adrenal (HPA) axis suppression, manifestations of Cushing's syndrome, hyperglycemia, and glucosuria in some patients.

Conditions which augment systemic absorption include the application of the more potent steroids, use over large surface areas, prolonged use, and the addition of occlusive dressings (See DOSAGE AND ADMINISTRATION).

Therefore, patients receiving a large dose of a potent topical steroid applied to a large surface area should be evaluated periodically for evidence of HPA axis suppression by using the urinary free cortisol and ACTH stimulation tests. If HPA axis suppression is noted, an attempt should be made to withdraw the drug, to reduce the frequency of application, or to substitute a less potent steroid.

Recovery of HPA axis function is generally prompt and complete upon discontinuation of the drug. Infrequently, signs and symptoms of steroid withdrawal may occur, requiring supplemental systemic corticosteroids.

Children may absorb proportionally larger amounts of topical corticosteroids and thus be more susceptible to systemic toxicity (See PRECAUTIONS—Pediatric Use). If irritation develops, topical corticosteroids should be discontinued and appropriate therapy instituted.

In the presence of dermatological infections, the use of an appropriate antifungal or antibacterial agent should be instituted. If a favorable response does not occur promptly, the corticosteroid should be discontinued until the infection has been adequately controlled.

PATIENT COUNSELING INFORMATION

Information for Patients: Patients using topical corticosteroids should receive the following information and instructions:

1. This medication is to be used as directed by the physician. It is for external use only. Avoid contact with the eyes.
2. Patients should be advised not to use this medication for any disorder other than that for which it was prescribed.
3. The treated skin area should not be bandaged or otherwise covered or wrapped as to be occlusive.
4. Patients should report any signs of local adverse reactions.
5. Parents of pediatric patients should be advised not to use tight-fitting diapers or plastic pants on a child being treated in the diaper area, as these garments may constitute occlusive dressings (See DOSAGE AND ADMINISTRATION).

LABORATORY TESTS

Laboratory tests: The following tests may be helpful in evaluating HPA axis suppression:

Urinary free cortisol test
ACTH stimulation test

CARCINOGENESIS AND MUTAGENESIS AND IMPAIRMENT OF FERTILITY

Carcinogenesis, Mutagenesis and Impairment of Fertility: Long-term animal studies have not been performed to evaluate the carcinogenic potential or the effect on fertility of topical corticosteroids.

Studies to determine mutagenicity with prednisolone and hydrocortisone have revealed negative results.

TERATOGENIC EFFECTS

Pregnancy Category C: Corticosteroids are generally teratogenic in laboratory animals when administered systemically at relatively low dosage levels. The more potent corticosteroids have been shown to be teratogenic after dermal application in laboratory animals. There are no adequate and well-controlled studies in pregnant women on teratogenic effects from topically applied corticosteroids. Therefore, topical corticosteroids should be used during pregnancy only if the potential benefit justifies the potential risk to the fetus. Drugs of this class should not be used extensively on pregnant patients, in large amounts, or for prolonged periods of time.

NURSING MOTHERS

Nursing Mothers: It is not known whether topical administration of corticosteroids could result in sufficient systemic absorption to produce detectable quantities in breast milk. Systemically administered corticosteroids are secreted into breast milk in quantities not likely to have a deleterious effect on the infant. Nevertheless, caution should be exercised when topical corticosteroids are administered to a nursing woman.

PEDIATRIC USE

Pediatric Use: Pediatric patients may demonstrate greater susceptibility to topical corticosteroid-induced HPA axis suppression and Cushing's syndrome than mature patients because of a larger skin surface area to body weight ratio.

Hypothalamic-pituitary-adrenal (HPA) axis suppression, Cushing's syndrome, and intracranial hypertension have been reported in children receiving topical corticosteroids. Manifestations of adrenal suppression in children include linear growth retardation, delayed weight gain, low plasma cortisol levels, and absence of response to ACTH stimulation. Manifestations of intracranial hypertension include bulging fontanelles, headaches, and bilateral papilledema.

Administration of topical corticosteroids to pediatric patients should be limited to the least amount compatible with an effective therapeutic regimen. Chronic corticosteroid therapy may interfere with the growth and development of children.

ADVERSE REACTIONS:

The following local adverse reactions are reported infrequently when Betamethasone Dipropionate products are used as recommended in the DOSAGE AND ADMINISTRATION section. These reactions are listed in an approximate decreasing order of occurrence: burning, itching, irritation, dryness, folliculitis, hypertrichosis, acneiform eruptions, hypopigmentation, perioral dermatitis, allergic contact dermatitis, maceration of the skin, secondary infections, skin atrophy, striae and miliaria.

Systemic absorption of topical corticosteroids has produced reversible hypothalamic-pituitary-adrenal (HPA) axis suppression, manifestations of Cushing's syndrome, hyperglycemia and glucosuria in some patients.

OVERDOSAGE:

Topically applied corticosteroids can be absorbed in sufficient amounts to produce systemic effects (See PRECAUTIONS).

DOSAGE AND ADMINISTRATION:

Apply a thin film of Betamethasone Dipropionate Cream or Ointment to the affected skin areas once daily. In some cases, twice daily dosage may be necessary.

Apply a few drops of Betamethasone Dipropionate Lotion to the affected skin areas and massage lightly until it disappears. Apply twice daily, in the morning and at night.

If an infection develops, appropriate antimicrobial therapy should be instituted.

Betamethasone Dipropionate products should not be used with occlusive dressings.

HOW SUPPLIED:

Betamethasone Dipropionate | Betamethasone Dipropionate | Betamethasone Dipropionate
Cream USP, 0.05% | Ointment USP, 0.05% | Lotion USP, 0.05%
is supplied as follows: | is supplied as follows: | is supplied as follows:
15 g tubes NDC 0168-0055-15 | 15 g tubes NDC 0168-0056-15 | 60 mL bottles NDC 0168-0057-60
45 g tubes NDC 0168-0055-46 | 45 g tubes NDC 0168-0056-46 | Shake well before using.

Store at 25°C, excursions permitted between 15° and 30°C. Protect from light and freezing.

E. FOUGERA & CO.
A division of
fougera
PHARMACETICALS INC.
Melville, New York 11747

46291737A
R06/2021
#74

PACKAGE LABEL – PRINCIPAL DISPLAY PANEL – 45g CREAM CONTAINER

NDC 0168-0055-46

FOUGERA®

BETAMETHASONE
DIPROPIONATE
CREAM USP, 0.05%
(Potency expressed as betamethasone)

Rx only

NET WT 45 grams

PACKAGE LABEL – PRINCIPAL DISPLAY PANEL – 45g CREAM CARTON

NDC 0168-0055-46

FOUGERA®

BETAMETHASONE DIPROPIONATE
CREAM USP, 0.05%
(Potency expressed as betamethasone)

Rx only

NET WT 45 grams

PACKAGE LABEL – PRINCIPAL DISPLAY PANEL – 15g OINTMENT CONTAINER

NDC 0168-0056-15

FOUGERA®

BETAMETHASONE
  DIPROPIONATE
  OINTMENT USP, 0.05%
  (Potency expressed as betamethasone)

Rx only

NET WT 15 grams

PACKAGE LABEL – PRINCIPAL DISPLAY PANEL – 15g OINTMENT CARTON

NDC 0168-0056-15

FOUGERA®

BETAMETHASONE DIPROPIONATE
OINTMENT USP, 0.05%
(Potency expressed as betamethasone)

Rx only

NET WT 15 grams

PACKAGE LABEL – PRINCIPAL DISPLAY PANEL – 60mL LOTION CONTAINER

NDC 0168-0057-60

FOUGERA®

BETAMETHASONE
DIPROPIONATE
LOTION USP, 0.05%
(Potency expressed as betamethasone)

60 mL

Rx only

PACKAGE LABEL – PRINCIPAL DISPLAY PANEL – 60mL LOTION CARTON

NDC 0168-0057-60

FOUGERA®

BETAMETHASONE
DIPROPIONATE
LOTION USP, 0.05%
(Potency expressed as
betamethasone)

60 mL

Rx only